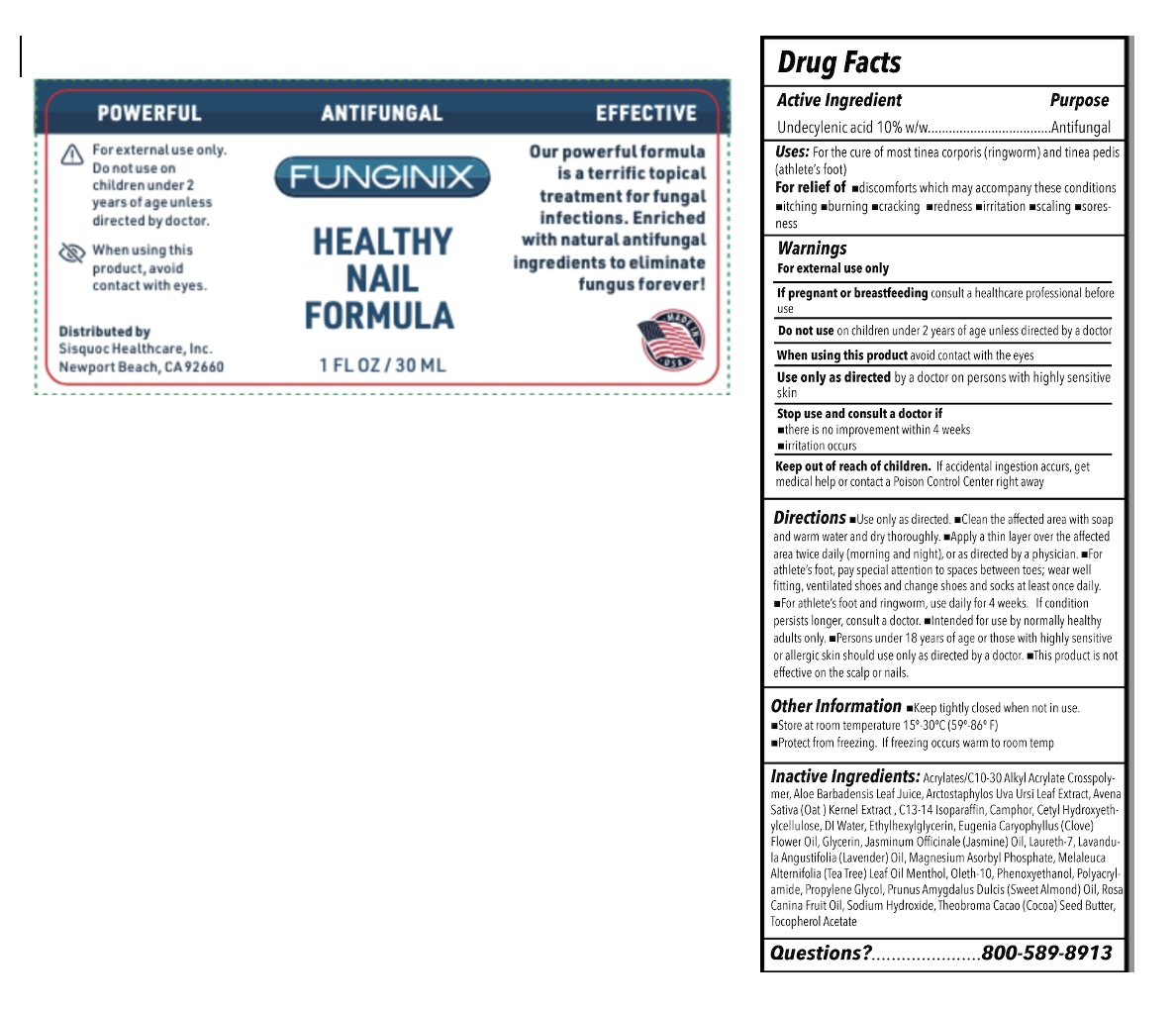 DRUG LABEL: FUNGINIX ANTI-FUNGAL TREATMENT
NDC: 71229-102 | Form: OINTMENT
Manufacturer: The Sisquoc Healthcare Corporation
Category: otc | Type: HUMAN OTC DRUG LABEL
Date: 20250421

ACTIVE INGREDIENTS: UNDECYLENIC ACID 10 g/100 mL
INACTIVE INGREDIENTS: WATER; ALMOND OIL; OLETH-10 PHOSPHATE; TROLAMINE; POLYSORBATE 20; BUTYL ACRYLATE/METHYL METHACRYLATE/METHACRYLIC ACID COPOLYMER (18000 MW); GLYCERIN; PROPYLENE GLYCOL; ARCTOSTAPHYLOS UVA-URSI WHOLE; OAT; PROPOLIS WAX; ALOE VERA LEAF; .ALPHA.-TOCOPHEROL ACETATE; CAMPHOR OIL; MENTHOL; TEA TREE OIL; LAVENDER OIL; JASMINUM OFFICINALE WHOLE; CLOVE OIL; COCOA BUTTER; ROSA CANINA FLOWER OIL; CETYL HYDROXYETHYLCELLULOSE (350000 MW); PHENOXYETHANOL; ETHYLHEXYLGLYCERIN

Sisquoc HC (as PLD) - FUNGINIX ANTI-FUNGAL TREATMENT (71229-102)

ACTIVE INGREDIENT

UNDECYLENIC ACID 10%

PURPOSE

ANTIFUNGAL

USES

- ANTI-FUNGAL TREATMENT

WARNINGS

FOR EXTERNAL USE ONLY.

DO NOT USE ON CHILDREN UNDER 2 YEARS OF AGE UNLESS DIRECTED BY A DOCTOR.

WHEN USING THIS PRODUCT AVOID CONTACT WITH THE EYES. IF CONTACT OCCURS, RINSE THE EYES VERY THOROUGHLY WITH WATER.

STOP USE AND ASK A DOCTOR IF IRRITATION OCCURS OR THERE IS NO IMPROVEMENT WITHIN 4 WEEKS.

KEEP OUT OF REACH OF CHILDREN. IF SWALLOWED, GET MEDICAL HELP OR CONTACT A POISON CONTROL CENTER RIGHT AWAY.

DIRECTIONS

- For the cure of most ringworm (tinea corporis) and athlete’s foot (tinea pedis). For relief of itching, scaling, cracking, burning, redness, soreness, irritation and discomforts which may accompany these conditions.
- Clean the affected area with soap and warm water and dry thoroughly. Apply a thin layer of FUNGINIX over the affected area twice daily (morning and night), or as directed by a physician. Allow 3-5 minutes for the solution to penetrate the skin and absorb fully into the surrounding tissue.
- FUNGINIX should be applied to cuticles, around nail edges and under nail tips where reachable with the applicator brush. This product is not intended to, nor will it, penetrate hard nail surfaces.
- For athlete’s foot, pay special attention to spaces between toes; wear well fitting, ventilated shoes and change shoes and socks at least once daily. For athlete’s foot and ringworm, use daily for 4 weeks. If condition persists longer, consult a doctor.
- Intended for use by normally healthy adults only. Persons under 18 years of age or those with highly sensitive or allergic skin should use only as directed by a doctor.

INACTIVE INGREDIENTS

Water, Prunus Amygdalus Dulcis (Sweet Almond) Oil, Oleth-10 Phosphate, Triethanolamine, Polysorbate 20, Acrylates Copolymer, Glycerin, Propylene Glycol, Uva Ursi (Bearberry) Extract, Beta-Glucan, Propolis Extract, Aloe Barbadensis Juice, Tocopheryl Acetate (Vitamin E), Camphor, Menthol, Melaleuca Alternifolia (Tea Tree) Leaf Oil, Lavandula Angustifolia (Lavender) Oil, Jasminum Offi cinale (Jasmine Oil,
Eugenia Caryophyllus (Clove) Flower Oil, Theobroma Cacao (Cocoa) Seed Butter, Rosa Canina (Rose Hip) Flower Oil, Cetyl Hydroxyethylcellulose, Ethylhexylglycerin, Phenoxyethanol

STORAGE AND HANDLING

Store between 20°c to 25°C (68° to 77°F)